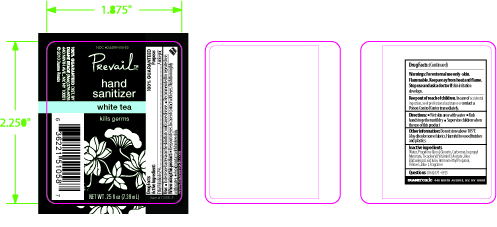 DRUG LABEL: Hand Sanitizer
NDC: 24488-005 | Form: SPRAY
Manufacturer: Creation's Garden Natural Products, Inc
Category: otc | Type: HUMAN OTC DRUG LABEL
Date: 20100412

ACTIVE INGREDIENTS: ALCOHOL 4.58 mL/7.39 mL
INACTIVE INGREDIENTS: Water; PROPYLENE GLYCOL; GLYCERIN; ISOPROPYL MYRISTATE; ALPHA-TOCOPHEROL ACETATE; ALOE VERA LEAF; AMINOMETHYLPROPANOL; FD&C YELLOW NO. 5

Drug Facts

ACTIVE INGREDIENT

Ethyl Alcohol 62%.................................Antiseptic

Uses

- To decrease bacteria on the skin that could cause disease.

- Recommended for repeated use.

Warnings

When using this product:

- Keep out of eyes. In case of contact with eyes, flush thoroughly with water
- Avoid contact with broken skin
- For external use only-skin
- Flammable. Keep away from heat and flame.
- Stop use and ask doctor if skin irritation develops

Keep out of reach of children

In case of accidental ingestion, seek professional assistance or contact a Poison Control Center immediately

Directions

- Wet skin area with product
- Rub hands together until dry
- supervise children with the use of this product

Other information

Do not store above 105°F. May discolor some fabrics. Harmful to wood finishes and plastics.

Inactive ingredients

Water, Propylene Glycol, Glycerin, Carbomer, Isopropyl Myristate, Tocopheryl (Vitamin E) Acetate, Aloe Barbadensis Leaf Juice, Aminomethyl Propanol, Yellow 5, Fragrance

Questions

(866) 375-6925